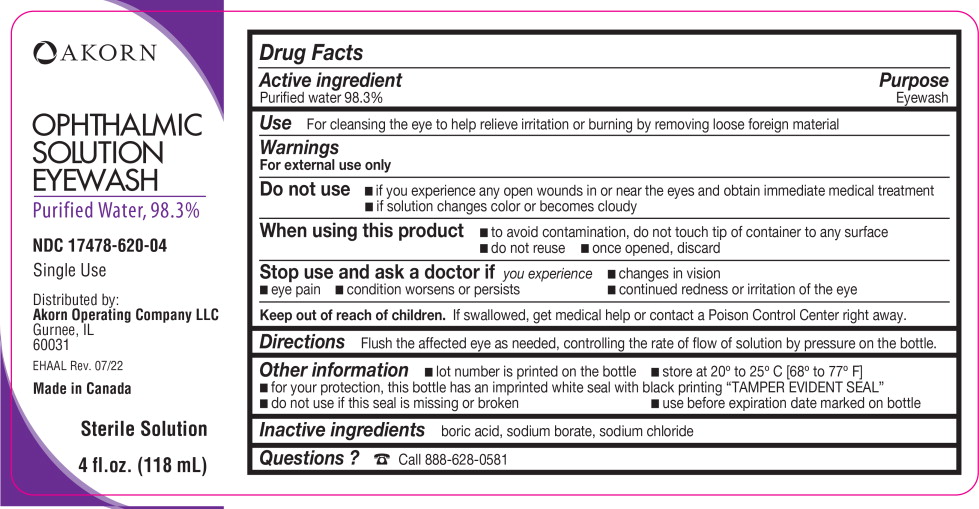 DRUG LABEL: Eyewash
NDC: 17478-620 | Form: SOLUTION
Manufacturer: Akorn
Category: otc | Type: HUMAN OTC DRUG LABEL
Date: 20220713

ACTIVE INGREDIENTS: Water 929 g/946 mL
INACTIVE INGREDIENTS: Boric Acid; Sodium Borate; Sodium Chloride

Drug Facts

Active ingredient

Purified water 98.3%

Purpose

Eyewash

Use

For cleansing the eye to help relieve irritation or burning by removing loose foreign material

Warnings

For external use only

Do not use

- if you experience any open wounds in or near the eyes and obtain immediate medical treatment
- if solution changes color or becomes cloudy

When using this product

- to avoid contamination, do not touch tip of container to any surface
- do not reuse
- once opened, discard

Stop use and ask a doctor if you experience

- changes in vision
- eye pain
- condition worsens or persists
- continued redness or irritation of the eye

Keep out of reach of children. If swallowed, get medical help or contact a Poison Control Center right away.

Directions

Flush the affected eye as needed, controlling the rate of flow of solution by pressure on the bottle.

Other information

- lot number is printed on the bottle
- store at 20° to 25° C [68° to 77° F]
- for your protection, this bottle has an imprinted white seal with black printing “TAMPER EVIDENT SEAL”
- do not use if this seal is missing or broken
- use before expiration date marked on bottle

Inactive ingredients

boric acid, sodium borate, sodium chloride

Questions?

Call 888-628-0581

Principal Display Panel Text for Container Label:

Akorn logo

OPHTHALMIC

SOLUTION

EYEWASH

Purified Water, 98.3%

NDC 17478-620-04

Single Use

Distributed by:

Akorn Operating Company LLC

Gurnee, IL

60031

EHAAL Rev. 07/22

Made in Canada

Sterile Solution

4 fl.oz. (118 mL)